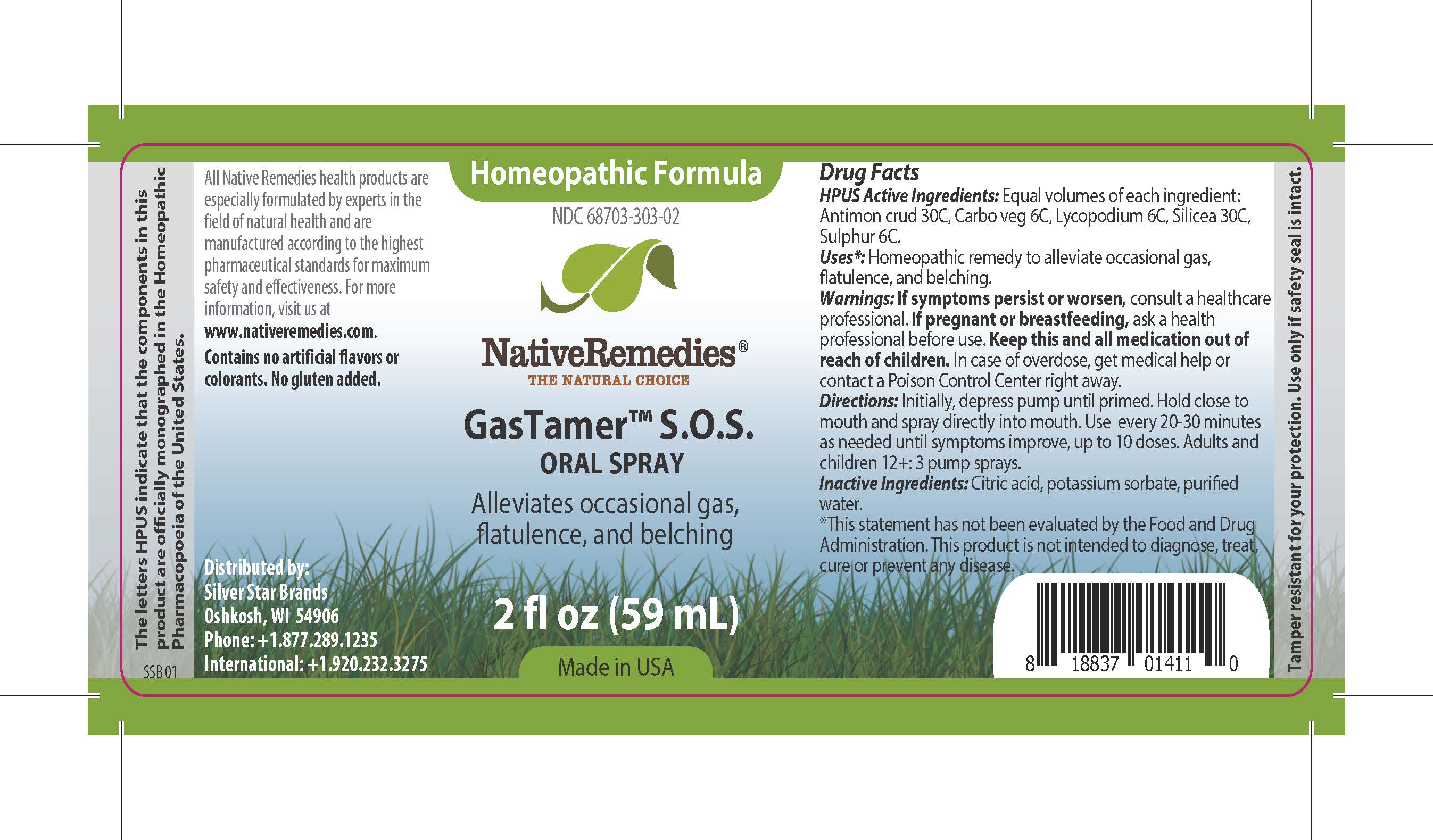 DRUG LABEL: GasTamer S.O.S.
NDC: 68703-303 | Form: SPRAY
Manufacturer: Silver Star Brands
Category: homeopathic | Type: HUMAN OTC DRUG LABEL
Date: 20230304

ACTIVE INGREDIENTS: SILICON DIOXIDE 30 [hp_C]/59 mL; ACTIVATED CHARCOAL 6 [hp_C]/59 mL; LYCOPODIUM CLAVATUM SPORE 6 [hp_C]/59 mL; ANTIMONY TRISULFIDE 30 [hp_C]/59 mL; SULFUR 6 [hp_C]/59 mL
INACTIVE INGREDIENTS: WATER; ANHYDROUS CITRIC ACID; POTASSIUM SORBATE

NativeRemedies® GasTamer™ S.O.S. Oral Spray

HPUS Active Ingredients:

Equal volumes of each ingredient: Antimon crud 30C, Carbo veg 6C, Lycopodium 6C, Silicea 30C, Sulphur 6C.

Uses*:

Homeopathic remedy to alleviate occasional gas, flatulence, and belching.

*This statement has not been evaluated by the Food and Drug Administration. This product is not intended to diagnose, treat, cure or prevent any disease.

Warnings:

If symptoms persist or worsen, consult a healthcare professional. If pregnant or breastfeeding, ask a health professional before use. Keep this and all medication out of reach of children. In case of overdose, get medical help or contact a Poison Control Center right away.

Directions:

Initially, depress pump until primed. Hold close to mouth and spray directly into mouth. Use every 20-30 minutes as needed until symptoms improve, up to 10 doses. Adults and children 12+: 3 pump sprays.

OTHER SAFETY INFORMATION

All Native Remedies health products are especially formulated by experts in the field of natural health and are manufactured according to the highest pharmaceutical standards for maximum safety and effectiveness. For more information, visit us at www.nativeremedies.com.

Contains no artificial flavors or colorants. No gluten added.

Inactive Ingredients:

Citric acid, potassium sorbate, purified water.

KEEP OUT OF REACH OF CHILDREN

Keep this and all medication out of reach of children. In case of overdose, get medical help or contact a Poison Control Center right away.

PREGNANCY OR BREAST FEEDING

If pregnant or breastfeeding, ask a health professional before use.

PURPOSE

Alleviates occasional gas, flatulence, and belching